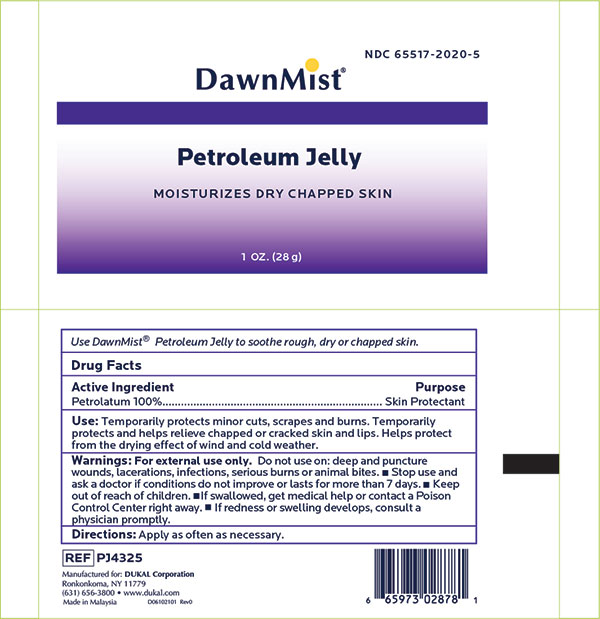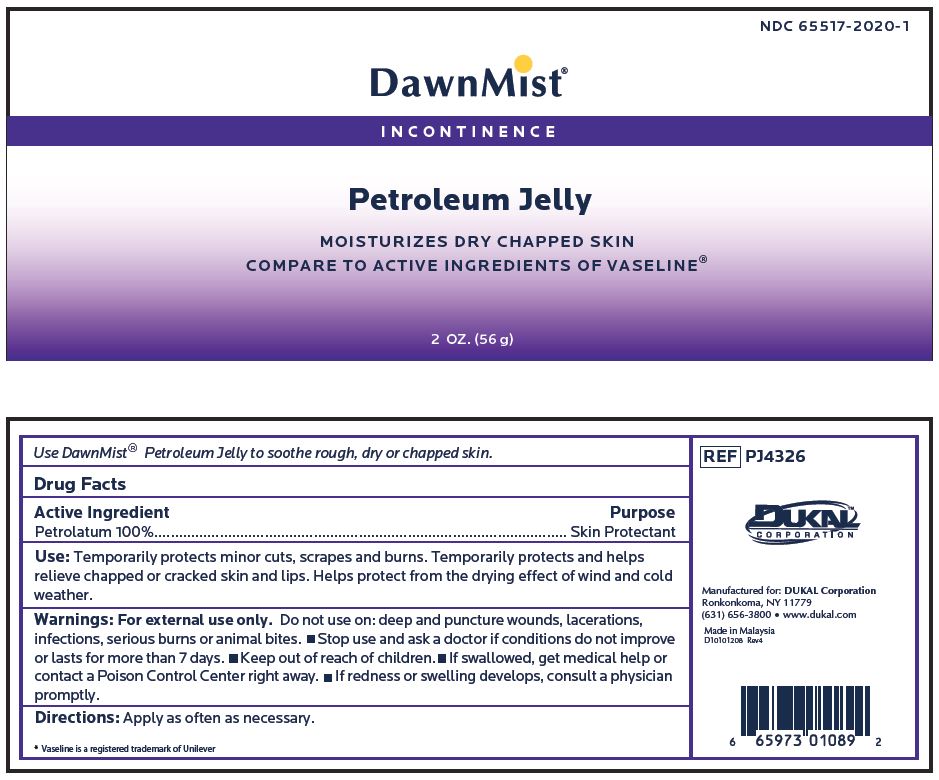 DRUG LABEL: Dawnmist Petroleum
NDC: 65517-2020 | Form: JELLY
Manufacturer: Dukal LLC
Category: otc | Type: HUMAN OTC DRUG LABEL
Date: 20240723

ACTIVE INGREDIENTS: PETROLATUM 100 g/100 g

Drug Facts

Active Ingredients

Petrolatum 100%

Purpose

Skin Protectant

Use:

Temporarily protects minor cuts, scrapes and burns. Temporarily protects and helps relieve chapped or cracked skin and lips. Helps protect from the drying effect of wind and cold weather.

Warnings:

For external use only. Do not use on: deep and puncture wounds lacerations or infections serious burns animal bites.

- Stop use and ask a doctor if conditions does not improve or lasts more than 7 days.

- Keep out of reach of children.
- If swallowed get medical help or contact Poison Control Center right away.
- If redness or swelling develops consult a physician promptly.

Directions:

Apply as often as necessary.

Principal Display Panel - Tube Label

NDC 65517-2020-1

DawnMist®
INCONTINENCE

Petroleum Jelly

MOISTURIZES DRY
CHAPPED SKIN

COMPARE TO ACTIVE INGREDIENTS
OF VASELINE®

2 oz. (56 g)

RECENT MAJOR CHANGES

Removed information from the directions section that is not applicable to the directions.

Principal Display Panel - 1oz Tube Label

NDC 65517-2020-5

DawnMist ®
INCONTINENCE

Petroleum Jelly

MOISTURIZES DRY CHAPPED SKIN

1 oz. (28 g)